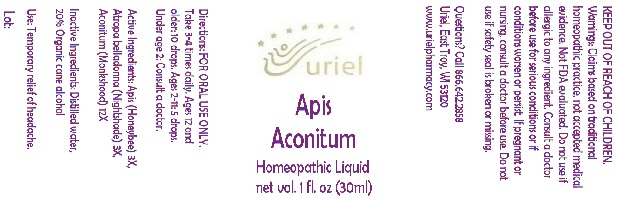 DRUG LABEL: Apis Aconitum
NDC: 48951-1042 | Form: LIQUID
Manufacturer: Uriel Pharmacy Inc.
Category: homeopathic | Type: HUMAN OTC DRUG LABEL
Date: 20191126

ACTIVE INGREDIENTS: APIS MELLIFERA 3 [hp_X]/1 mL; ATROPA BELLADONNA 3 [hp_X]/1 mL; ACONITUM NAPELLUS 12 [hp_X]/1 mL
INACTIVE INGREDIENTS: WATER; ALCOHOL

Apis Aconitum

INDICATIONS AND USAGE

Directions: FOR ORAL USE ONLY.

DOSAGE AND ADMINISTRATION

Take 3-4 times daily. Ages 12 and older: 10 drops. Ages 2-11: 5 drops. Under age 2: Consult a doctor.

ACTIVE INGREDIENT

Active Ingredients: Apis (Honeybee) 3X, Atropa belladonna (Nightshade) 3X, Aconitum (Monkshood) 12X

Inactive Ingredients: Distilled water, 20% Organic cane alcohol

PURPOSE

Use: Temporary relief of headache.

KEEP OUT OF REACH OF CHILDREN.

WARNINGS

Warnings: Claims based on traditional homeopathic practice, not accepted medical evidence. Not FDA evaluated. Do not use if allergic to any ingredient. Consult a doctor before use for serious conditions or if conditions worsen or persist. If pregnant or nursing, consult a doctor before use. Do not use if safety seal is broken or missing.

QUESTIONS

Questions? Call 866.642.2858 Uriel, East Troy, WI 53120 www.urielpharmacy.com